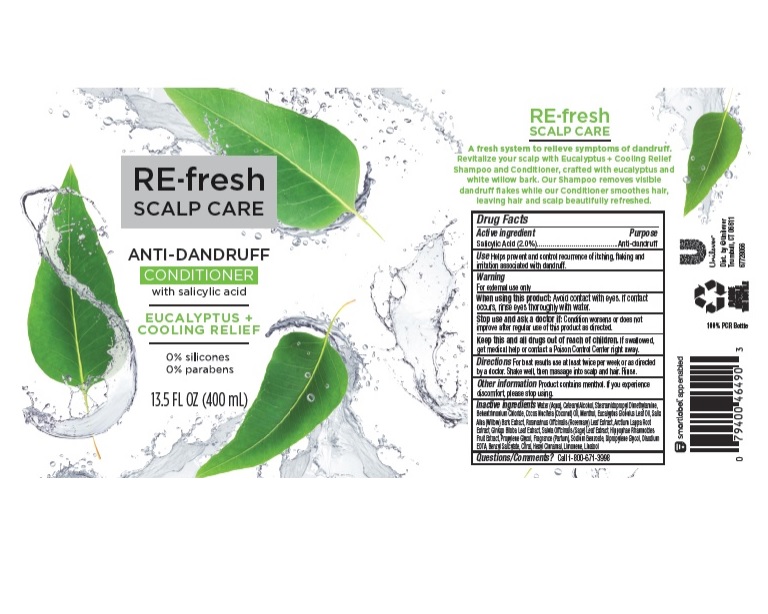 DRUG LABEL: RE-fresh Scalp Care
NDC: 64942-1638 | Form: LIQUID
Manufacturer: Conopco, Inc. d/b/a/ Unilever
Category: otc | Type: HUMAN OTC DRUG LABEL
Date: 20221207

ACTIVE INGREDIENTS: SALICYLIC ACID 2 g/100 mL
INACTIVE INGREDIENTS: WATER; COCAMIDOPROPYL BETAINE; CETOSTEARYL ALCOHOL; STEARAMIDOPROPYL DIMETHYLAMINE; BEHENTRIMONIUM CHLORIDE; COCONUT OIL; MENTHOL; EUCALYPTUS OIL; ARCTIUM LAPPA ROOT; GINKGO; PROPYLENE GLYCOL; SODIUM BENZOATE; DIPROPYLENE GLYCOL; EDETATE DISODIUM ANHYDROUS; BENZYL SALICYLATE; CITRAL; .ALPHA.-HEXYLCINNAMALDEHYDE; LIMONENE, (+)-; LINALOOL, (+/-)-

RE-fresh Scalp Care Eucalyptus + Cooling Relief Anti-Dandruff Conditioner

RE-FRESH SCALP CARE EUCALYPTUS + COOLING RELIEF ANTI-DANDRUFF CONDITIONER - salicylic acid liquid

RE-fresh Scalp Care Eucalyptus + Cooling Relief Anti-Dandruff Conditioner

Drug Facts

Active ingredient

Salicylic Acid (2.0%)

Purpose

Anti-dandruff

Use

Helps prevent and control recurrence of itching, flaking and irritation associated with dandruff.

Warnings

For external use only
When using this product Avoid contact with eyes. If contact occurs, rinse eyes thoroughly with water.
Stop use and ask a doctor if Condition worsens or does not improve after regular use of this product as directed.

KEEP OUT OF REACH OF CHILDREN

Keep this and all drugs out of reach of children. If swallowed, get medical help or contact a Poison Control Center right away.

Directions

For best results use at least twice per week or as directed by a doctor. Massage into scalp and hair. Rinse.

Inactive Ingredients

Water (Aqua), Cetearyl Alcohol, Stearamidopropyl Dimethylamine, Behentrimonium Chloride, Cocos Nucifera (Coconut) Oil, Menthol, Eucalyptus Globulus Leaf Oil, Salix Alba (Willow) Bark Extract, Rosmarinus Officinalis (Rosemary) Leaf Extract, Arctium Lappa Root Extract, Ginkgo Biloba Leaf Extract, Salvia Officinalis (Sage) Leaf Extract, Hippophae Rhamnoides Fruit Extract, Propylene Glycol, Fragrance (Parfum), Sodium Benzoate, Dipropylene Glycol, Disodium EDTA, Benzyl Salicylate. Citral, Hexyl Cinnamal, Limonene, Linalool.

Questions, comments?

Call toll-free 1-800-671-3998